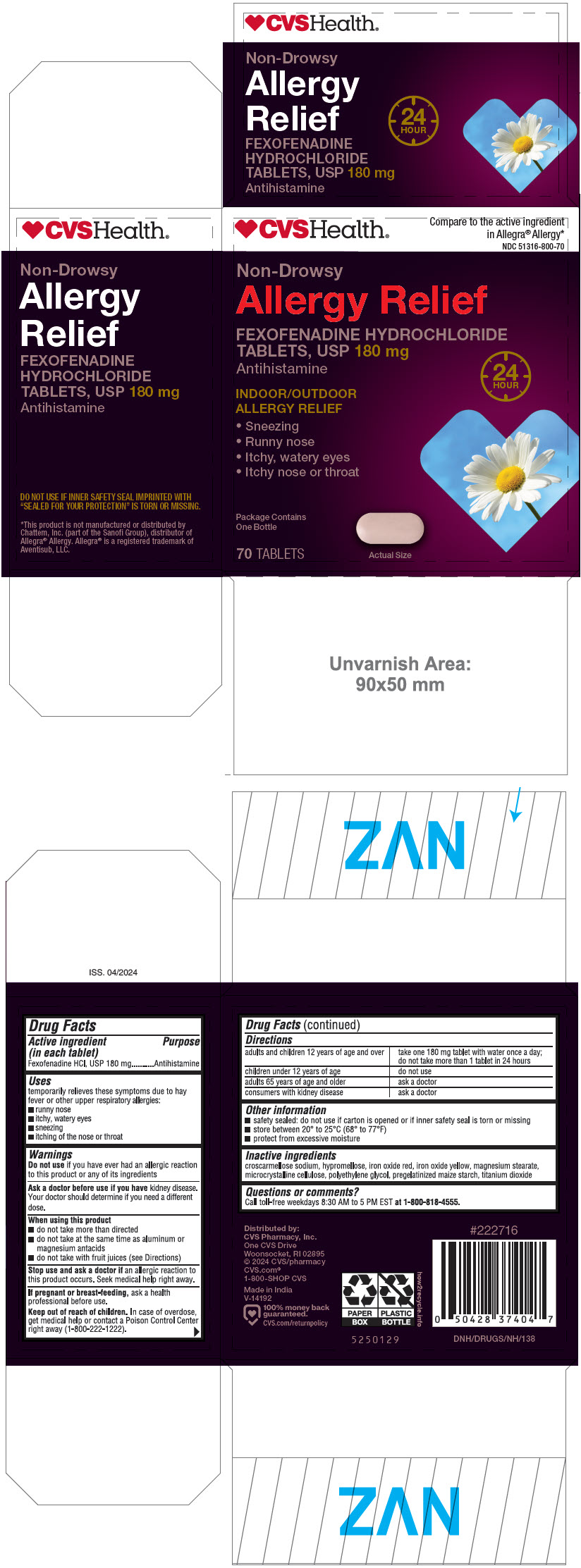 DRUG LABEL: FEXOFENADINE HYDROCHLORIDE
NDC: 51316-800 | Form: TABLET
Manufacturer: CVS PHARMACY, INC
Category: otc | Type: HUMAN OTC DRUG LABEL
Date: 20240524

ACTIVE INGREDIENTS: FEXOFENADINE HYDROCHLORIDE 180 mg/1 1
INACTIVE INGREDIENTS: CROSCARMELLOSE SODIUM; STARCH, CORN; MAGNESIUM STEARATE; HYPROMELLOSE, UNSPECIFIED; TITANIUM DIOXIDE; POLYETHYLENE GLYCOL 400; FERRIC OXIDE RED; FERRIC OXIDE YELLOW

Fexofenadine Hydrochloride Tablets, USP 180 mg

Drug Facts

Active ingredient (in each tablet)

Fexofenadine HCl, USP 180 mg

Purpose

Antihistamine

Uses

temporarily relieves these symptoms due to hay fever or other upper respiratory allergies:

- runny nose
- itchy, watery eyes
- sneezing
- itching of the nose or throat

Warnings

Do not use if you have ever had an allergic reaction to this product or any of its ingredients

Ask a doctor before use if you have kidney disease. Your doctor should determine if you need a different dose.

When using this product

- do not take more than directed
- do not take at the same time as aluminum or magnesium antacids
- do not take with fruit juices (see Directions)

Stop use and ask a doctor if an allergic reaction to this product occurs. Seek medical help right away.

PREGNANCY OR BREAST FEEDING

If pregnant or breast-feeding, ask a health professional before use.

Keep out of reach of children. In case of overdose, get medical help or contact a Poison Control Center right away (1-800-222-1222).

Directions

adults and children 12 years of age and over | take one 180 mg tablet with water once a day; do not take more than 1 tablet in 24 hours
children under 12 years of age | do not use
adults 65 years of age and older | ask a doctor
consumers with kidney disease | ask a doctor

Other information

- safety sealed: do not use if carton is opened or if inner safety seal is torn or missing
- store between 20° to 25°C (68° to 77°F)
- protect from excessive moisture

Inactive ingredients

croscarmellose sodium, hypromellose, iron oxide red, iron oxide yellow, magnesium stearate, microcrystalline cellulose, polyethylene glycol, pregelatinized maize starch, titanium dioxide

Questions or comments?

Call toll-free weekdays 8:30 AM to 5 PM EST at 1-800-818-4555.

Distributed by:
CVS Pharmacy, Inc.
One CVS Drive
Woonsocket, RI 02895

PRINCIPAL DISPLAY PANEL - 180 mg Tablet Bottle Carton

CVS Health®

Compare to the active ingredient
in Allegra® Allergy*

NDC 51316-800-70

Non-Drowsy

Allergy Relief

FEXOFENADINE HYDROCHLORIDE
TABLETS, USP 180 mg
Antihistamine

24
HOUR

INDOOR/OUTDOOR
ALLERGY RELIEF

- Sneezing
- Runny nose
- Itchy, watery eyes
- Itchy nose or throat

Package Contains
One Bottle

70 TABLETS

Actual Size